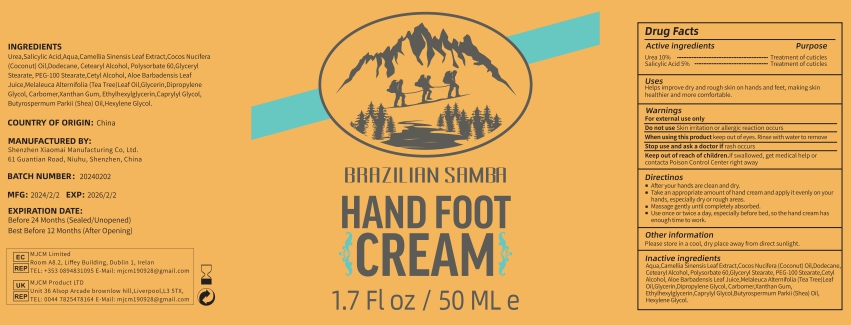 DRUG LABEL: HAND FOOT
NDC: 83872-265 | Form: CREAM
Manufacturer: Shenzhen Xiaomai Manufacturing Co., Ltd.
Category: otc | Type: HUMAN OTC DRUG LABEL
Date: 20240628

ACTIVE INGREDIENTS: SALICYLIC ACID 2.5 mg/50 g; 1,1-DIPHENYLUREA 50 mg/50 g
INACTIVE INGREDIENTS: DODECANE; POLYSORBATE 60; XANTHAN GUM; CAMELLIA SINENSIS FLOWER; COCONUT OIL; CETYL ALCOHOL; CETEARYL GLUCOSIDE; GLYCERYL STEARATE SE

Active ingredients

Urea10%
Salicylic Acid5%

Purpose

Helps improve dry and rough skin on hands and feet, making skin healthier and more comfortable.

Uses

Helps improve dry and rough skin on hands and feet, making skin healthier and more comfortable.

Warnings

For external use only
Do not use Skin irritation or allergic reaction occurs.
When using this product keep out of eyes. Rinse with water to remove.
Stop use and ask a doctor if rash occurs
Keep out of reach of children.If swallowed, get medical help or contacta Poison Control Center right away.

Do not use

For external use only
Do not use Skin irritation or allergic reaction occurs.

When using this product keep out of eyes. Rinse with water to remove.

Stop use and ask a doctor if rash occurs

Keep out of reach of children.If swallowed, get medical help or contacta Poison Control Center right away.

Ask Doctor

Stop use and ask a doctor if rash occurs

Directions

After your hands are clean and dry
Take an appropriate amount of hand cream and apply it evenly on your hands, especially dry or rough areas.
Massage gently until completely absorbed.
Use once or twice a day, especially before bed, so the hand cream has enough time to work.

Other information

Please store in a cool, dry place away from direct sunlight.

Inactive ingredients

Aqua,Camellia Sinensis Leaf Extract,Cocos Nucifera (Coconut) Oil,Dodecane, Cetearyl Alcohol, Polysorbate 60,Glyceryl Stearate, PEG-100 Stearate,Cetyl Alcohol, Aloe Barbadensis Leaf Juice,Melaleuca Alternifolia (Tea Tree)Leaf Oil,Glycerin,Dipropylene Glycol, Carbomer,Xanthan Gum, Ethylhexylglycerin,Caprylyl Glycol,Butyrospermum Parkii (Shea) Oil, Hexylene Glycol.